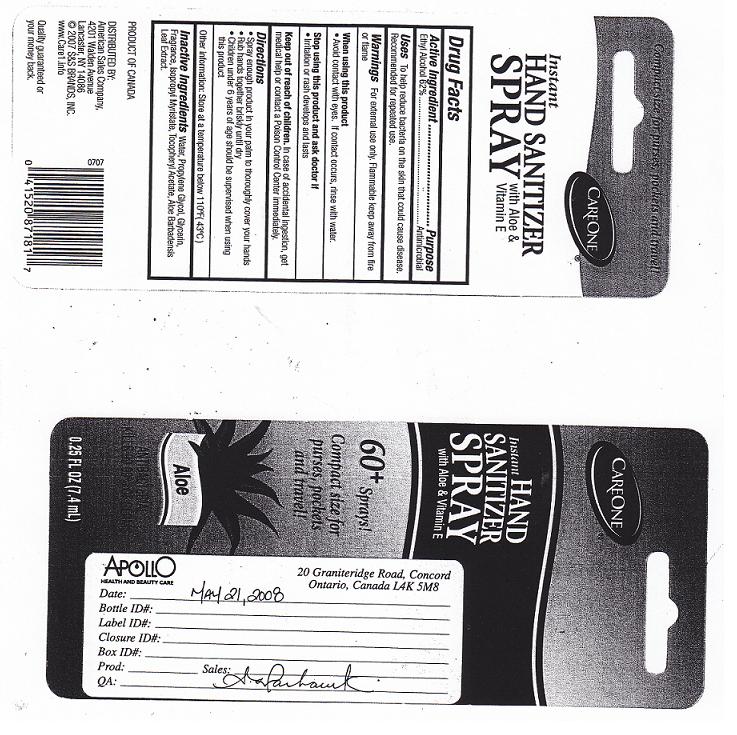 DRUG LABEL: SANITIZER
NDC: 41520-235 | Form: LIQUID
Manufacturer: AMERICAN SALES
Category: otc | Type: HUMAN OTC DRUG LABEL
Date: 20110506

ACTIVE INGREDIENTS: ALCOHOL 62 mL/100 mL
INACTIVE INGREDIENTS: WATER; PROPYLENE GLYCOL; GLYCERIN; ISOPROPYL MYRISTATE; .ALPHA.-TOCOPHEROL ACETATE, D-; ALOE VERA LEAF

Drug Facts

ACTIVE INGREDIENT

ETHYL ALCOHOL 62 PERCENT

PURPOSE

ANTIMICROBIAL

USES

TO HELP REDUCE BACTERIA ON THE SKIN THAT COULD CAUSE DISEASE. RECOMMENDED FOR REPEATED USE.

WARNINGS

FOR EXTERNAL USE ONLY. FLAMMABLE KEEP AWAY FROM FIRE OR FLAME.

WHEN USING THIS PRODUCT

AVOID CONTACT WITH EYES. IF CONTACT OCCURS, RINSE WITH WATER.

STOP USING THIS PRODUCT AND ASK DOCTOR IF

IRRITATION OR RASH DEVELOPS AND LASTS.

KEEP OUT OF REACH OF CHILDREN

IN CASE OF ACCIDENTAL INGESTION, GET MEDICAL HELP OR CONTACT A POISON CONTROL CENTER IMMEDIATELY.

DIRECTIONS

SPRAY ENOUGH PRODUCT IN YOUR PALM TO THOROUGHLY COVER YOUR HANDS.

RUB HANDS TOGETHER BRISKLY UNTIL DRY.

CHILDREN UNDER 6 YEARS OF AGE SHOULD BE SUPERVISED WHEN USING THIS PRODUCT.

OTHER INFORMATION

STORE AT A TEMPERATURE BELOW 110 DEGREES FAHRENHEIT (43 DEGREES CELSIUS).

INACTIVE INGREDIENTS

WATER, PROPYLENE GLYCOL, GLYCERIN, FRAGRANCE, ISOPROPYL MYRISTATE, TOCOPHERYL ACETATE, ALOE BARBADENSIS LEAF EXTRACT.